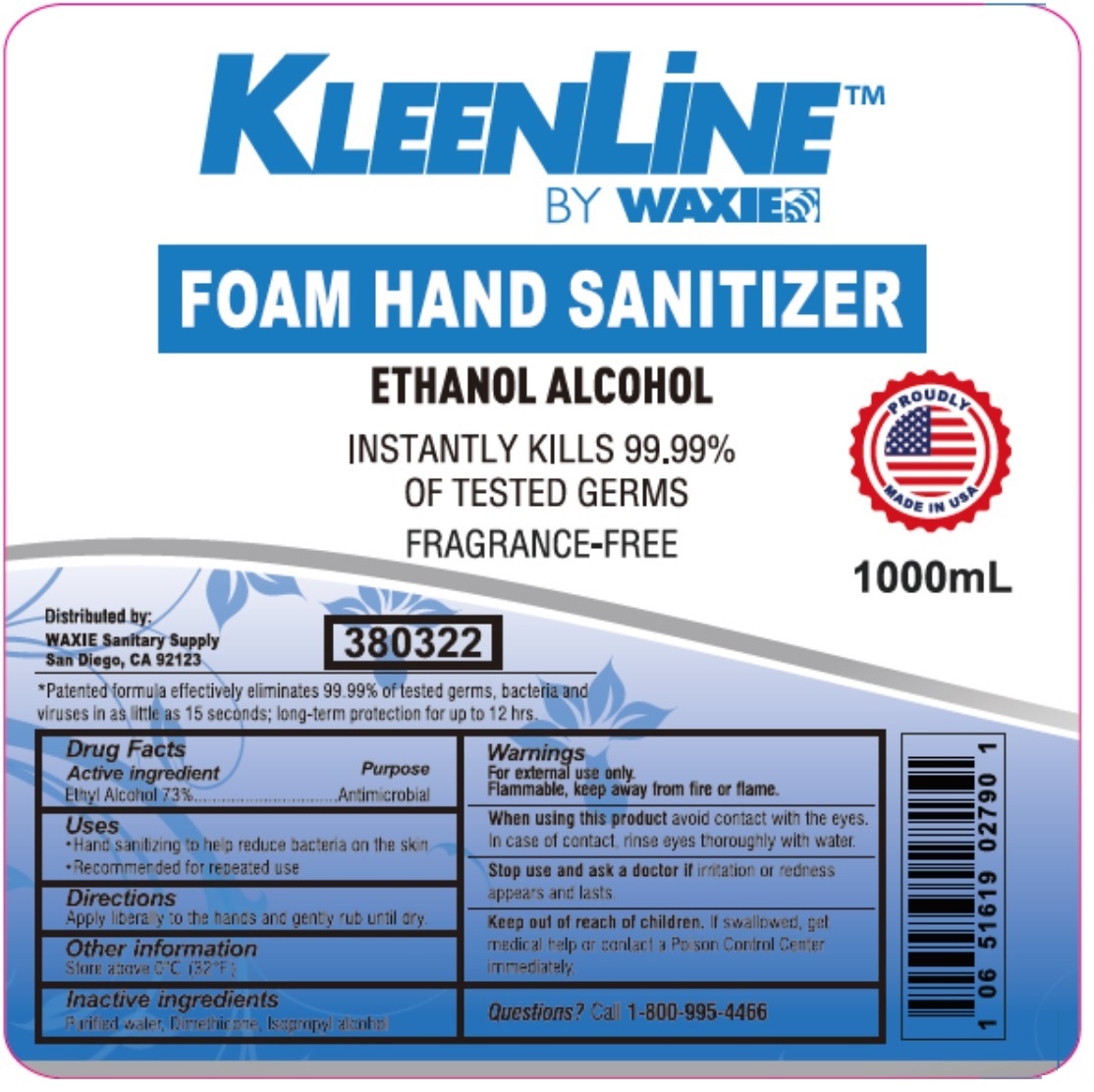 DRUG LABEL: KLEENLINE
NDC: 78168-628 | Form: LIQUID
Manufacturer: Teh Tung Corporation
Category: otc | Type: HUMAN OTC DRUG LABEL
Date: 20201006

ACTIVE INGREDIENTS: ALCOHOL 73 mL/100 mL
INACTIVE INGREDIENTS: WATER; DIMETHICONE; ISOPROPYL ALCOHOL

KLEENLiNE™ FOAM HAND SANITIZER

Active ingredient

Ethyl Alcohol 73%

Purpose

Antimicrobial

Uses

• Hand sanitizing to help reduce bacteria on the skin

• Recommended for repeated use

Directions

Apply liberally to the hands and gently rub until dry.

Other information

Store above 0°C (32°F)

Inactive ingredients

Purified water, Dimethicone, Isopropyl alcohol

Warnings

For external use only.

Flammable, keep away from fire or flame.

When using this product avoid contact with the eyes. In case of contact, rinse eyes thoroughly with water.

Stop use and ask a doctor if irritation or redness appears and lasts.

Keep out of reach of children. If swallowed, get medical help or contact a Poison Control Center immediately.

Questions? Call 1-800-995-4466

BY WAXIE

FOAM HAND SANITIZER

ETHANOL ALCOHOL

INSTANTLY KILLS 99.99% OF TESTED GERMS

FRAGRANCE-FREE

PROUDLY MADE IN USA

Distributed by:

WAXIE Sanitary Supply
San Diego, CA 92123

*Patented formula effectively eliminates 99.99% of tested germs, bacteria and viruses in as little as 15 seconds; long-term protection for up to 12 hrs.